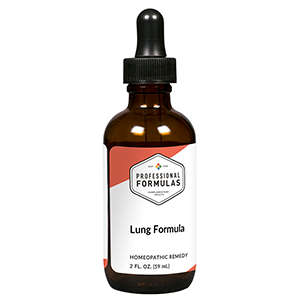 DRUG LABEL: Lung Formula
NDC: 63083-2104 | Form: LIQUID
Manufacturer: Professional Complementary Health Formulas
Category: homeopathic | Type: HUMAN OTC DRUG LABEL
Date: 20190815

ACTIVE INGREDIENTS: STEMONA TUBEROSA ROOT 1 [hp_X]/59 mL; GLYCYRRHIZA INFLATA ROOT 1 [hp_X]/59 mL; TRICHOSANTHES KIRILOWII SEED 1 [hp_X]/59 mL; LAMINARIA JAPONICA 1 [hp_X]/59 mL; PUMICE 1 [hp_X]/59 mL; SARGASSUM PALLIDUM 1 [hp_X]/59 mL; IMPERATA CYLINDRICA ROOT 1 [hp_X]/59 mL; MORUS ALBA LEAF 1 [hp_X]/59 mL; DESCURAINIA SOPHIA SEED 1 [hp_X]/59 mL; PRUNUS ARMENIACA SEED 1 [hp_X]/59 mL; ALPINIA OXYPHYLLA FRUIT 1 [hp_X]/59 mL; HOUTTUYNIA CORDATA WHOLE 1 [hp_X]/59 mL
INACTIVE INGREDIENTS: ALCOHOL; WATER

C104

ACTIVE INGREDIENTS

all the following at 1X:
Bai-Bu
Gan-Cao
Gua-Lou
Hai-Dai
Hai-Fu-Shi
Hai-Zao
Mao-Gen
Sang-Ye
Ting-Li-Zi
Xing-Ren
Yi-Yi-Ren
Yu-Xing-Cao

QUESTIONS

Professional Formulas

PO Box 2034 Lake Oswego, OR 97035

INDICATIONS

For the temporary relief of cough, shortness of breath, wheezing, or hoarseness.*

PURPOSE

*Claims based on traditional homeopathic practice, not accepted medical evidence. Not FDA evaluated.

WARNINGS

Severe or persistent symptoms may be serious. Consult a doctor promptly. Keep out of the reach of children. In case of overdose, get medical help or contact a poison control center right away. If pregnant or breastfeeding, ask a healthcare professional before use.

Keep out of the reach of children.

PREGNANCY OR BREAST FEEDING

If pregnant or breastfeeding, ask a healthcare professional before use.

DIRECTIONS

Place drops under tongue 30 minutes before/after meals. Adults and children 12 years and over: Take 10 drops up to 3 times per day. Consult a physician for use in children under 12 years of age.

OTHER INFORMATION

Tamper resistant. If seal is broken, do not use. After opening, close container tightly and store at room temperature away from heat.

INACTIVE INGREDIENTS

20% ethanol, purified water.

LABEL

Est 1985

Professional Formulas

Complementary Health

Lung Formula

Homeopathic Remedy

2 FL. OZ. (59 mL)